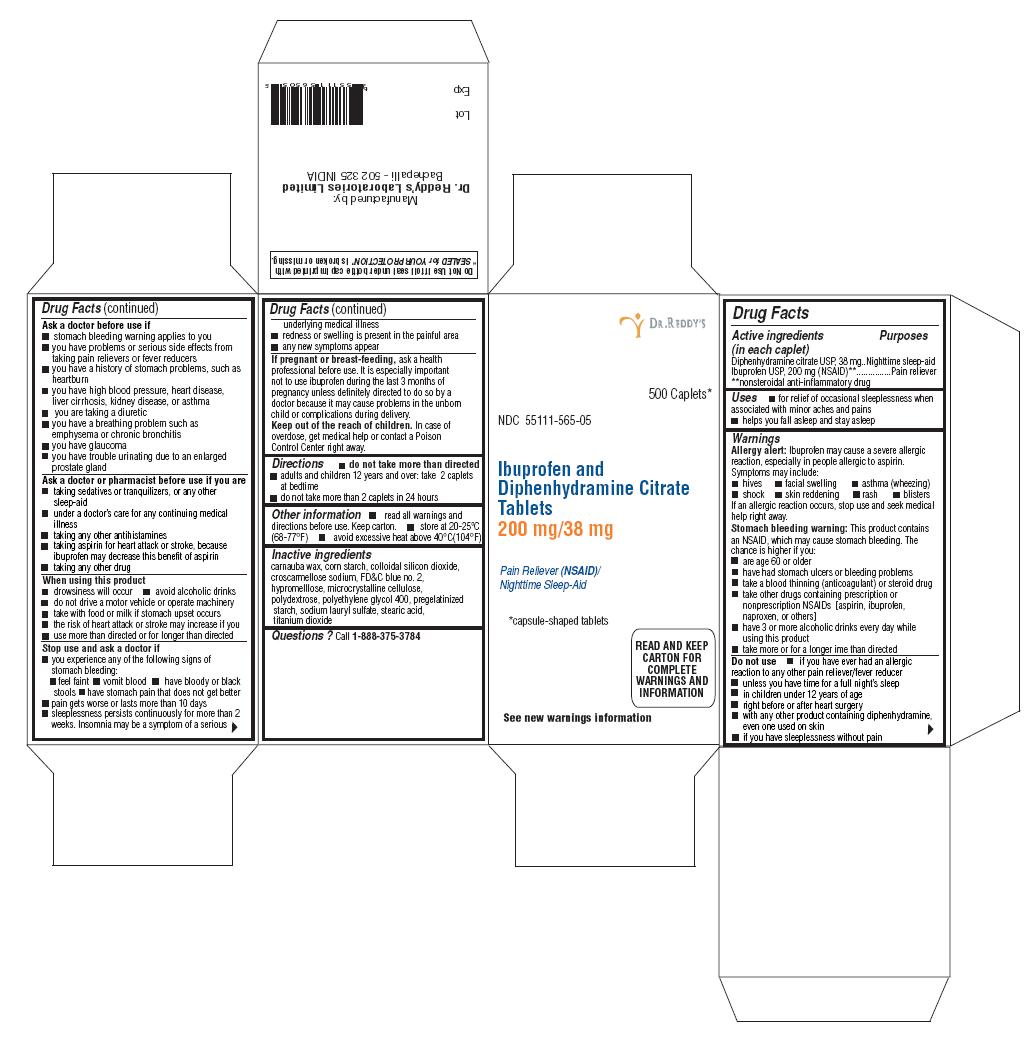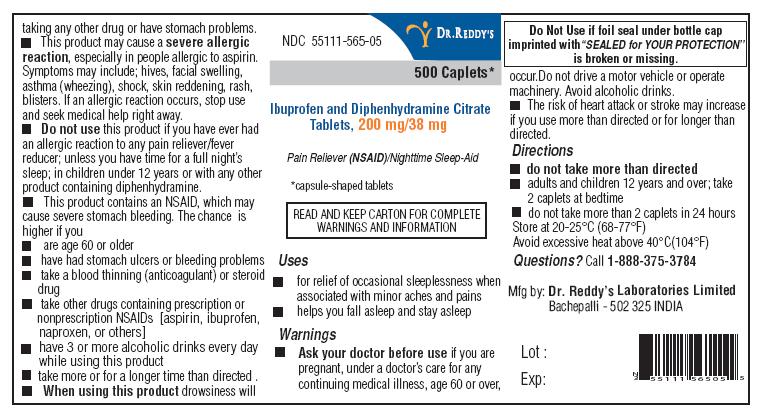 DRUG LABEL: Ibuprofen and Diphenhydramine Citrate
NDC: 55111-565 | Form: TABLET
Manufacturer: Dr. Reddy's Laboratories Limited
Category: otc | Type: HUMAN OTC DRUG LABEL
Date: 20181205

ACTIVE INGREDIENTS: Ibuprofen 200 mg/1 1; Diphenhydramine Citrate 38 mg/1 1
INACTIVE INGREDIENTS: carnauba wax; STARCH, CORN; Silicon Dioxide; croscarmellose sodium; FD&C blue no. 2; CELLULOSE, MICROCRYSTALLINE; hypromelloses; polydextrose; polyethylene glycol 400; sodium lauryl sulfate; stearic acid; titanium dioxide

Ibuprofen and Diphenhydramine Citrate Tablets

ACTIVE INGREDIENTS (IN EACH CAPLET)

Diphenhydramine citrate USP, 38 mg

Ibuprofen USP, 200 mg (NSAID)**

* capsule-shaped tablets

**nonsteroidal anti-inflammatory drug

PURPOSES

Nighttime sleep-aid

Pain reliever

USES

- for relief of occasional sleeplessness when associated with minor aches and pains
- helps you fall asleep and stay asleep

WARNINGS

Allergy alert:

Ibuprofen may cause a severe allergic reaction, especially in people allergic to aspirin. Symptoms may include:

- hives
- facial swelling
- asthma (wheezing)
- shock
- skin reddening
- rash
- blisters

If an allergic reaction occurs, stop use and seek medical help right away.

Stomach bleeding warning:

This product contains an NSAID, which may cause stomach bleeding. The chance is higher if you:

- are age 60 or older
- have had stomach ulcers or bleeding problems
- take a blood thinning (anticoagulant) or steroid drug
- take other drugs containing an NSAID [aspirin, ibuprofen, naproxen, or others]
- have 3 or more alcoholic drinks every day while using this product
- take more or for a longer time than directed

Do not use

- if you have ever had an allergic reaction to any other pain reliever/fever reducer
- unless you have time for a full night's sleep
- in children under 12 years of age
- right before or after heart surgery
- with any other product containing diphenhydramine, even one used on skin
- if you have sleeplessness without pain.

Ask a doctor before use if

- stomach bleeding warning applies to you
- you have problems or serious side effects from taking pain relievers or fever reducers
- you have a history of stomach problems, such as heartburn
- you have high blood pressure, heart disease, liver cirrhosis, kidney disease, or asthma
- you are taking a diuretic
- you have a breathing problem such as emphysema or chronic bronchitis
- you have glaucoma
- you have trouble urinating due to an enlarged prostate gland

Ask a doctor or pharmacist before use if you are

- taking sedatives or tranquilizers, or any other sleep-aid
- under a doctor’s care for any continuing medical illness
- taking any other antihistamines
- taking aspirin for heart attack or stroke, because ibuprofen may decrease this benefit of aspirin
- taking any other drug

When using this product

- drowsiness will occur
- avoid alcoholic drinks
- do not drive a motor vehicle or operate machinery
- take with food or milk if stomach upset occurs
- the risk of heart attack or stroke may increase if you use more than directed or for longer than directed

Stop use and ask a doctor if

- you experience any of the following signs of stomach bleeding:
- feel faint
- vomit blood
- have bloody or black stools
- have stomach pain that does not get better
- pain gets worse or lasts more than 10 days
- sleeplessness persists continuously for more than 2 weeks. Insomnia may be a symptom of a serious underlying medical illness.
- redness or swelling is present in the painful area
- any new symptoms appear

If pregnant or breast-feeding,

ask a health professional before use. It is especially important not to use ibuprofen during the last 3 months of pregnancy unless definitely directed to do so by a doctor because it may cause problems in the unborn child or complications during delivery.

Keep out of the reach of children.

In case of overdose, get medical help or contact a Poison Control Center right away.

DIRECTIONS

- do not take more than directed
- adults and children 12 years and over: take 2 caplets at bedtime.
- do not take more than 2 caplets in 24 hours

OTHER INFORMATION

- read all warnings and directions before use. Keep carton.
- store at 20-25°C (68-77°F)
- avoid excessive heat above 40°C (104°F)

INACTIVE INGREDIENTS

carnauba wax, corn starch, colloidal silicon dioxide, croscarmellose sodium, FD&C blue no. 2, hypromelllose, microcrystalline cellulose, polydextrose, polyethylene glycol 400, pregelatinized starch, sodium lauryl sulfate, stearic acid, titanium dioxide

QUESTIONS?

Call 1-888-375-3784

Do Not Use if foil seal under bottle cap imprinted with“SEALED for YOUR PROTECTION” is broken or missing.

Manufactured by:

Dr. Reddy’s Laboratories Limited

Bachepalli – 502 325 INDIA.

PRINCIPAL DISPLAY PANEL

Container:

PACKAGE LABEL

Container carton